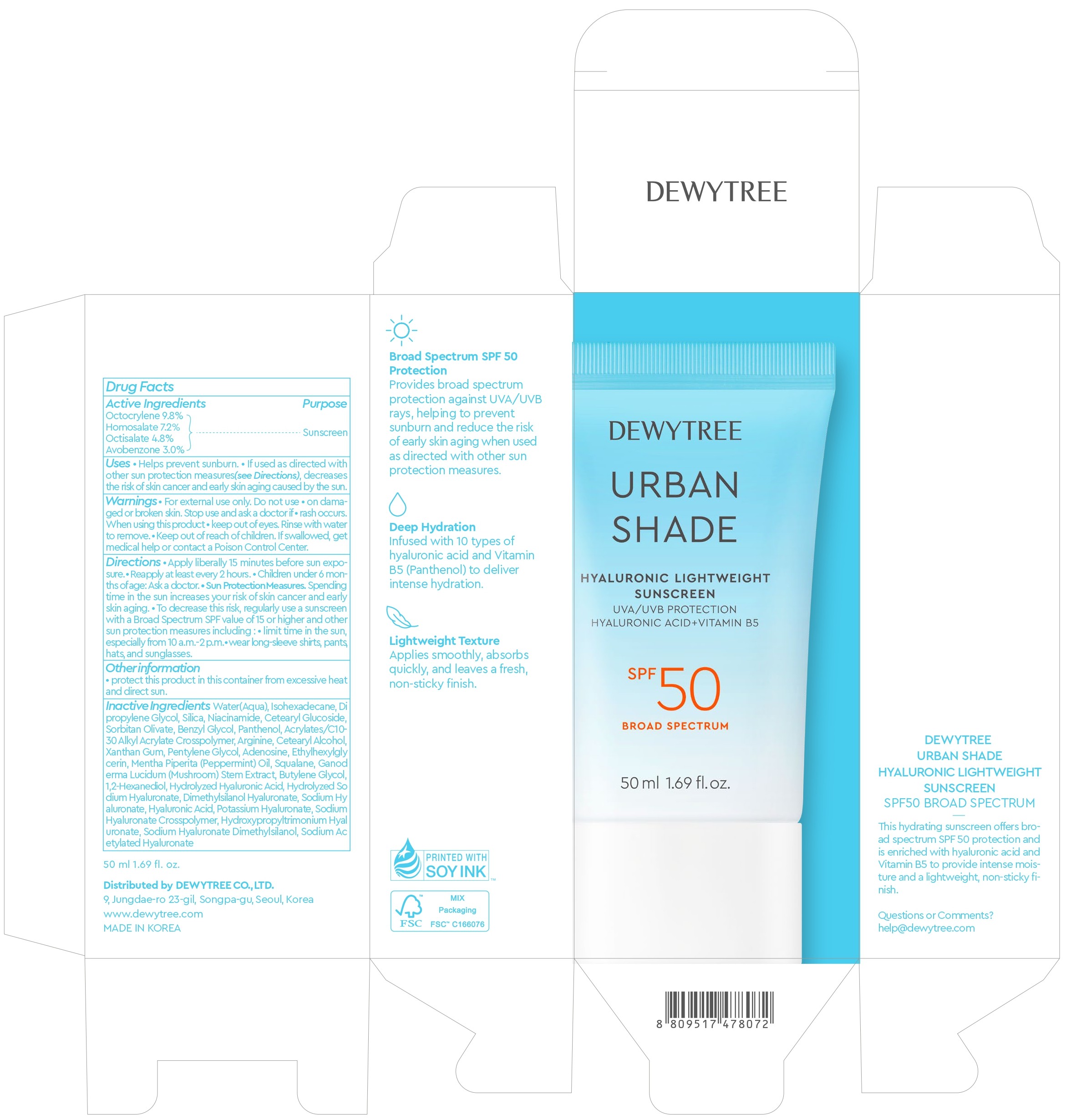 DRUG LABEL: DEWYTREE URBAN SHADE HYALURONIC LIGHTWEIGHT SUNSCREEN
NDC: 73071-101 | Form: CREAM
Manufacturer: DEWYTREE CO. ,LTD
Category: otc | Type: HUMAN OTC DRUG LABEL
Date: 20251021

ACTIVE INGREDIENTS: OCTISALATE 2.4 g/50 mL; HOMOSALATE 3.6 g/50 mL; OCTOCRYLENE 4.9 g/50 mL; AVOBENZONE 1.5 g/50 mL
INACTIVE INGREDIENTS: ARGININE; SODIUM ACETYLATED HYALURONATE; ACRYLATES/C10-30 ALKYL ACRYLATE CROSSPOLYMER (60000 MPA.S); SQUALANE; CETEARYL ALCOHOL; NIACINAMIDE; ADENOSINE; BUTYLENE GLYCOL; DIMETHYLSILANOL HYALURONATE; PANTHENOL; DIPROPYLENE GLYCOL; SILICA; PENTYLENE GLYCOL; ETHYLHEXYLGLYCERIN; 1,2-HEXANEDIOL; SORBITAN OLIVATE; BENZYL GLYCOL; GANODERMA LUCIDUM STEM; XANTHAN GUM; SODIUM HYALURONATE; WATER; ISOHEXADECANE; MENTHA PIPERITA (PEPPERMINT) OIL; HYALURONIC ACID; CETEARYL GLUCOSIDE

73071-101 DEWYTREE URBAN SHADE HYALURONIC LIGHTWEIGHT SUNSCREEN

ACTIVE INGREDIENT

Octocrylene 9.8%

Homosalate 7.2%

Octisalate 4.8%

Avobenzone 3.0%

PURPOSE

Sunscreen

INDICATIONS AND USAGE

■ Helps prevent sunburn. ■ if used as directed with other sun protection measures (see Directions), decreases the risk of skin cancer and early skin aging caused by the sun.

WARNINGS

■ For external use only.

Do not use ■ on damaged or broken skin.

Stop use and ask a doctor if ■ rash occurs.

When using this product ■ keep out of eyes. Rinse with water to remove.

■ Keep out of reach of children. If swallowed, get medical help or contact a Poison Control Center.

Directions

■ Apply liberally 15 minutes before sun exposure. ■ Reapply at least every 2 hours. ■ Children under 6 months of age: Ask a doctor. ■ Sun Protection Measures. Spending time in the sun increases your risk of skin cancer and early skin aging. ■ To decrease this risk, regularly use a sunscreen with a Broad Spectrum SPF value of 15 or higher and other sun protection measures including: ■ limit time in the sun, especially from 10a.m.-2 p.m. wear long-sleeve shirts, pants, hats, and sunglasses.

OTHER SAFETY INFORMATION

■ protect this product in this container from excessive heat and direct sun.

INACTIVE INGREDIENT

Water(Aqua), Isohexadecane, Dipropylene Glycol, Silica, Niacinamide, Cetearyl Glucoside, Sorbitan Olivate, Benzyl Glycol, Panthenol, Acrylates/C10-30 Alkyl Acrylate Crosspolymer, Arginine, Cetearyl Alcohol, Xanthan Gum, Pentylene Glycol, Adenosine, Ethylhexylgly cerin, Mentha Piperita (Peppermint) Oil, Squalane, Ganoderma Lucidum (Mushroom) Stem Extract, Butylene Glycol, 1,2-Hexanediol, Hydrolyzed Hyaluronic Acid, Hydrolyzed Sodium Hyaluronate, Dimethylsilanol Hyaluronate, Sodium Hyaluronate, Hyaluronic Acid, Potassium Hyaluronate, Sodium Hyaluronate Crosspolymer, Hydroxypropyltrimonium Hyaluronate, Sodium Hyaluronate Dimethylsilanol, Sodium Acetylated Hyaluronate